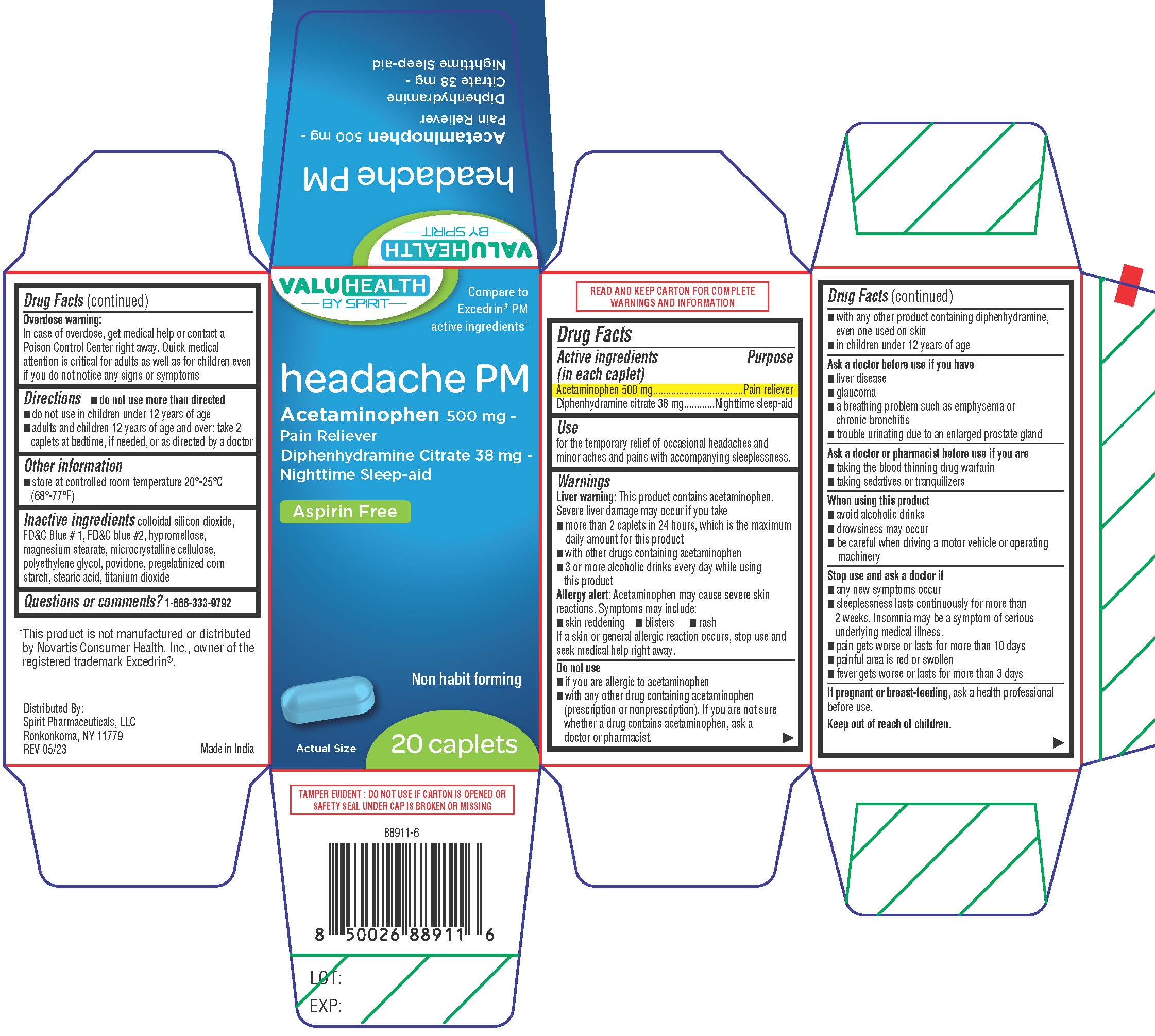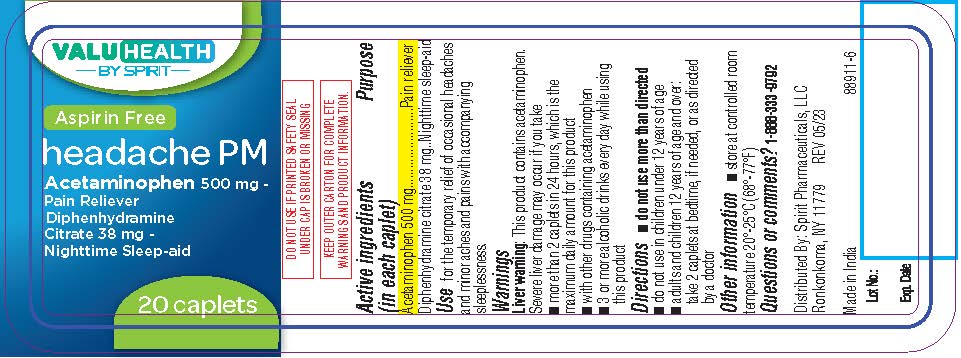 DRUG LABEL: Assured Headache PM (Aspirin Free)
NDC: 68210-4135 | Form: TABLET, COATED
Manufacturer: Spirit Pharmaceutical LLC
Category: otc | Type: HUMAN OTC DRUG LABEL
Date: 20241230

ACTIVE INGREDIENTS: ACETAMINOPHEN 500 mg/1 1; DIPHENHYDRAMINE CITRATE 38 mg/1 1
INACTIVE INGREDIENTS: POLYETHYLENE GLYCOL, UNSPECIFIED; POVIDONE K30; STARCH, CORN; STEARIC ACID; TITANIUM DIOXIDE; SILICON DIOXIDE; FD&C BLUE NO. 1; FD&C BLUE NO. 2; HYPROMELLOSES; MAGNESIUM STEARATE; CELLULOSE, MICROCRYSTALLINE

Headache PM (Aspirin Free)

Drug Facts

ACTIVE INGREDIENT

Active ingredients (in each caplet) | Purpose
Acetaminophen 500 mg | Pain reliever
Diphenhydramine citrate 38 mg | Nighttime sleep-aid

Uses

for the temporary relief of occasional headaches and minor aches and pains with accompanying sleeplessness.

Warnings

Liver warning

This product contains acetaminophen. Severe liver damage may occur if you take

- more than 2 caplets in 24 hours, which is the maximum daily amount
- with other drugs containing acetaminophen
- 3 or more alcoholic drinks every day while using this product

Allergy alert

Acetaminophen may cause severe skin reactions. Symptoms may include:

- skin reddening
- blisters
- rash

If a skin or general allergic reaction occurs, stop use and seek medical help right away.

Do not use

- if you are allergic to acetaminophen
- with any other drug containing acetaminophen (prescription or nonprescription). If you are not sure whether a drug contains acetaminophen, ask a doctor or pharmacist.
- with any other product containing diphenhydramine, even one used on skin
- in children under 12 years of age

Ask a doctor before use if you have

- liver disease
- glaucoma
- a breathing problem such as emphysema or chronic bronchitis
- trouble urinating due to an enlarged prostate gland

Ask a doctor or pharmacist before use if you are

- taking the blood thinning drug warfarin
- taking sedatives or tranquilizers

When using this product

- avoid alcoholic drinks
- drowsiness may occur
- be careful when driving a motor vehicle or operating machinery

Stop use and ask a doctor if

- any new symptoms occur
- sleeplessness lasts continuously for more than 2 weeks. Insomnia may be a symptom of serious underlying medical illness.
- pain gets worse or lasts more than 10 days
- painful area is red or swollen
- fever gets worse or lasts more than 3 days

PREGNANCY OR BREAST FEEDING

If pregnant or breast-feeding, ask a health professional before use.

Keep out of reach of children.

Overdose warning

In case of overdose, get medical help or contact a Poison Control Center right away. Quick medical attention is critical for adults as well as for children even if you do not notice any signs or symptoms

Directions

- do not use more than directed
- do not use in children under 12 years of age
- adults and children 12 years of age and over: take 2 caplets at bedtime, if needed, or as directed by a doctor

Other information

- store at controlled room temperature 20°-25°C (68°-77°F)
- read all product information before using. Keep this box for important information.

Inactive ingredients

colloidal silicon dioxide, FD&C Blue # 1, FD&C blue #2, hypromellose, magnesium stearate, microcrystalline cellulose, polyethylene glycol, povidone, pregelatinized corn starch, stearic acid, titanium dioxide

Questions or comments?

1-888-333-9792

PRINCIPAL DISPLAY PANEL

Headache PM
Acetaminophen 500 mg - Pain Reliever
Diphenhydramine Citrate 38 mg - Nighttime Sleep-aid
Aspirin Free

Non habit forming

20 Caplets